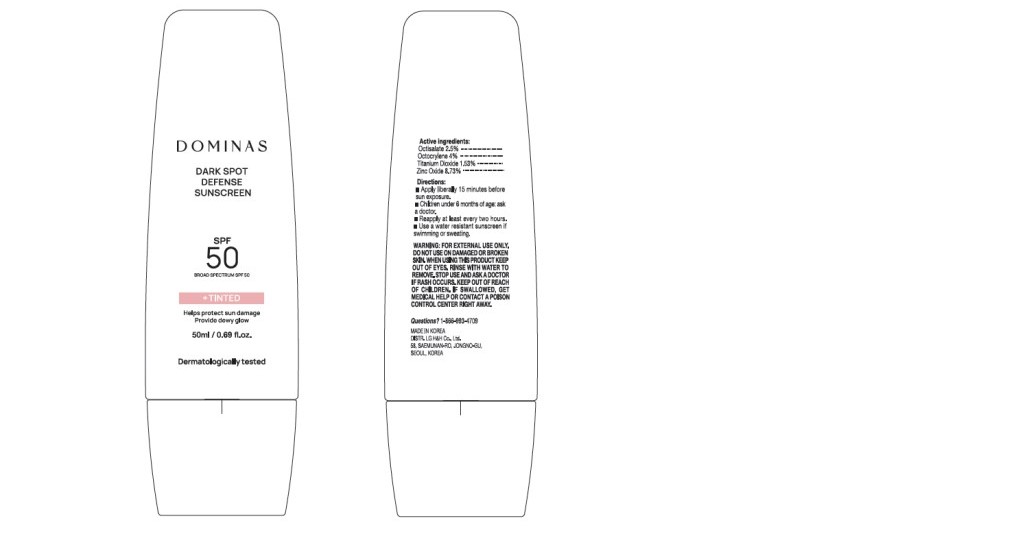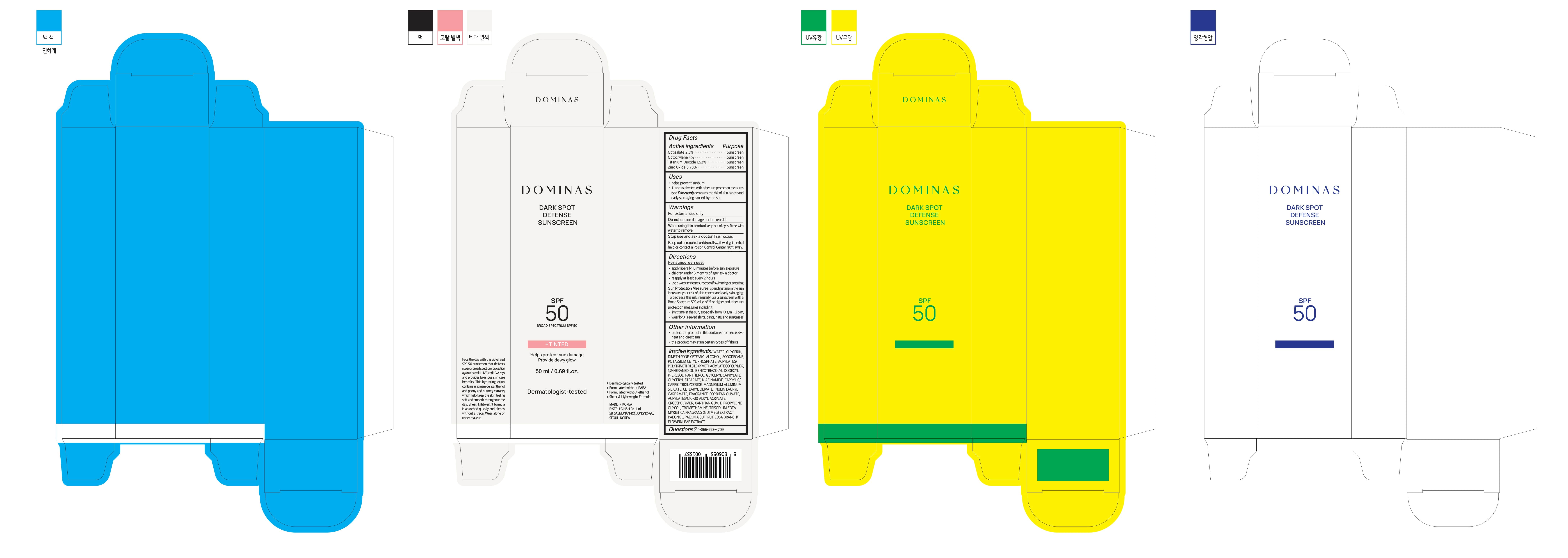 DRUG LABEL: DOMINAS DARK SPOT TINTED SUNSCREEN
NDC: 53208-302 | Form: CREAM
Manufacturer: LG H&H CO., LTD.
Category: otc | Type: HUMAN OTC DRUG LABEL
Date: 20250324

ACTIVE INGREDIENTS: OCTISALATE 2.5 g/100 g; TITANIUM DIOXIDE 1.53 g/100 g; OCTOCRYLENE 4 g/100 g; ZINC OXIDE 8.73 g/100 g
INACTIVE INGREDIENTS: DICAPRYLYL CARBONATE; NUTMEG; ORANGE TERPENES; DIPROPYLENE GLYCOL; GLYCERIN; CI 77491; ISOHEXADECANE; MAGNESIUM SULFATE; ALUMINUM MONOSTEARATE; ALUMINA; ETHYLHEXYLGLYCERIN; STEARYL GLYCYRRHETINATE; GLYCERYL CAPRYLATE; PEG-30 DIPOLYHYDROXYSTEARATE; TRIETHOXYCAPRYLYLSILANE; MICA; CI 77492; TOCOPHEROL; 1,2-HEXANEDIOL; HYDROXYCITRONELLAL; TRIETHOXYSILYLETHYL POLYDIMETHYLSILOXYETHYL HEXYL DIMETHICONE; CI 77499; DISTEARDIMONIUM HECTORITE; HEXYL LAURATE; WATER; CYCLOPENTASILOXANE; DIPHENYLSILOXY PHENYL TRIMETHICONE; CHRYSIN; SORBITAN OLIVATE; CAPRYLIC/CAPRIC TRIGLYCERIDE; PANTHENOL; CAMELLIA SINENSIS LEAF; LINALOOL; MORINGA OLEIFERA SEED OIL

Active Ingredients

Octisalate 2.5%

Octocrylene 4%

Titanium Dioxide 1.53%

Zinc Oxide 8.73%

Purpose

Sunscreen

Uses

- helps prevent sunburn
- if used as directed with other sun protection measures (see Directions),decreases the risk of skin cancer and early skin aging caused by the sun

Warning

For external use only.

Do not use on damaged or broken skin.

When Using

When using this product keep out of eyes. Rinse with water to remove.

Stop use and ask a doctor if rash occurs.

Keep out of reach of children

DOSAGE AND ADMINISTRATION

If swallowed, get medical help or contact a Poison Control Center right away.

Directions

For sunscreen use:

- apply liberally 15 minutes before sun exposure
- children under 6 months of age: ask a doctor
- reapply at least every 2 hours
- use a water resistant sunscree nif swimming or sweating

- Sun Protection Measures: Spending time in the sun increases your risk of skin cancer and early skin aging. To decrease this risk, regularly use a sunscreen with a Broad Spectrum SPF value of 15 or higher and other sun protection measures including:
- limit time in the sun, especially from 10 a.m.-2p.m.
- wear long-sleeved shirts, pants, hats and sunglasses

Other Information

- protect the product in this container from excessive heat and direct sun
- the product may stain certain types of fabrics

Questions?

1-866-993-4709

Inactive Ingredients

WATER, DICAPRYLYL CARBONATE, HEXYL LAURATE, DIPROPYLENE GLYCOL, SORBITAN OLIVATE, GLYCERIN, CYCLOPENTASILOXANE, ISOHEXADECANE, DISTEARDIMONIUM HECTORITE, PANTHENOL, CAPRYLIC/CAPRIC TRIGLYCERIDE, GLYCERYL CAPRYLATE, MAGNESIUM SULFATE, PEG-30 DIPOLYHYDROXYSTEARATE, FRAGRANCE, TRIETHOXYCAPRYLYLSILANE, ALUMINUM STEARATE, ALUMINA, MICA, ETHYLHEXYLGLYCERIN, STEARYL GLYCYRRHETINATE, IRON OXIDES(CI 77492), MYRISTICA FRAGRANS (NUTMEG) EXTRACT, IRON OXIDES(CI 77491), IRON OXIDES(CI 77499), MORINGA OLEIFERA SEED OIL, DIPHENYLSILOXY PHENYL TRIMETHICONE, TOCOPHEROL, TRIETHOXYSILYLETHYL POLYDIMETHYLSILOXYETHYL HEXYL DIMETHICONE, CHRYSIN, 1,2-HEXANEDIOL, CAMELLIA SINENSIS LEAF EXTRACT, HYDROXYCITRONELLAL, LIMONENE, LINALOOL